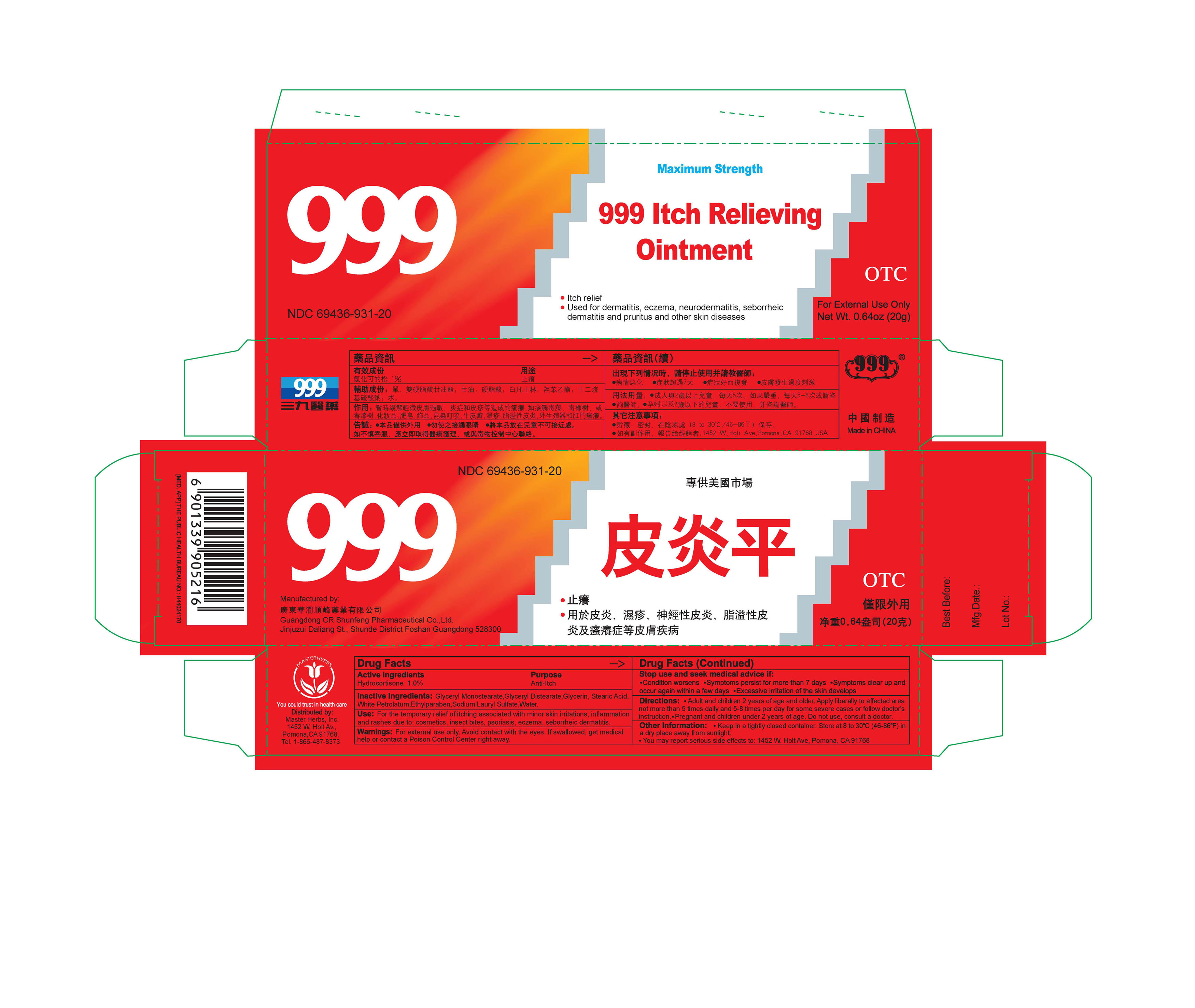 DRUG LABEL: 999 ITCH RELIEVING
NDC: 69436-931 | Form: OINTMENT
Manufacturer: Guangdong CR. Shunfeng Pharmaceutical Co Ltd
Category: otc | Type: HUMAN OTC DRUG LABEL
Date: 20161114

ACTIVE INGREDIENTS: HYDROCORTISONE 1 g/100 g
INACTIVE INGREDIENTS: GLYCERYL MONOSTEARATE; GLYCERYL DISTEARATE; GLYCERIN; STEARIC ACID; PETROLATUM; ETHYLPARABEN; SODIUM LAURYL SULFATE; WATER

999 ITCH RELIEVING OINTMENT

ACTIVE INGREDIENTS

Hydrocortisone 1.0%

Purpose

Anti-Itch

Use

For the temporary relief of itching associated with minor skin irritations, inflammation and rashes due to: cosmetics, insect bites, psoriasis, eczema, seborrheic dermatitis.

Warnings

For external use only. Avoid contact with the eyes. If swallowed, get medical help or contact a Poison Control Center right away.

Stop use and seek medical advice if

Condition worsens. Symptoms persist for more than 7 days. Symptoms clear up and occur again within a few days. Excessive irritation of the skin develops.

Directions

Adult and children 2 years of age and older. Apply liberally to affected area not more than 5 times daily and 5-8 times per day for some severe cases or follow doctor's instruction.

PREGNANCY OR BREAST FEEDING

Pregnant and children under 2 years of age. Do not use, consult a doctor.

Other Information

Keep in a tightly closed container. Store at 8 to 30 ℃ (46-86℉) in a dry place away from sunlight.

You may report serious side effects to: 1452 W. Holt Ave, Pomona, CA 91768

Inactive Ingredients

Glyceryl Monostearate, Glyceryl Distearate, Glycerin, Stearic Acid, White Petrolatum, Ethylparaben, Sodium Lauryl Sulfate, Water

Manufactured By Guangdong CR. Shunfeng Pharmaceutical Co.; Ltd.

Jinjuzu, Dalinag Street, Shunde District, Foshan, Guangdong, China 528300

Distributed by Master Herbs Inc.

1452 W. Holt Ave, Pomona, CA 91768

(866)487-8373